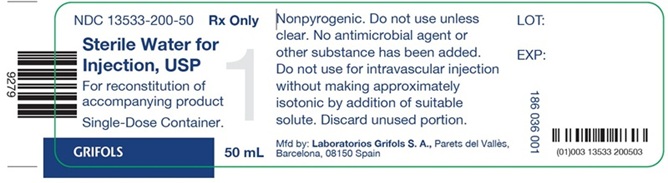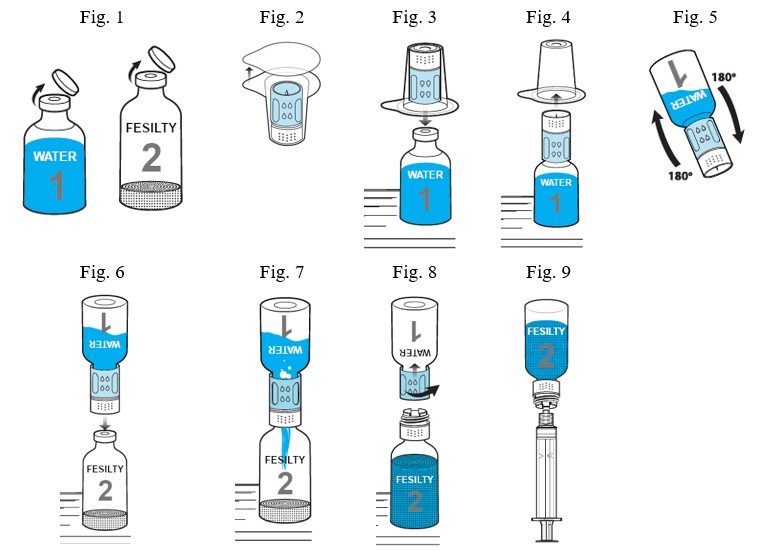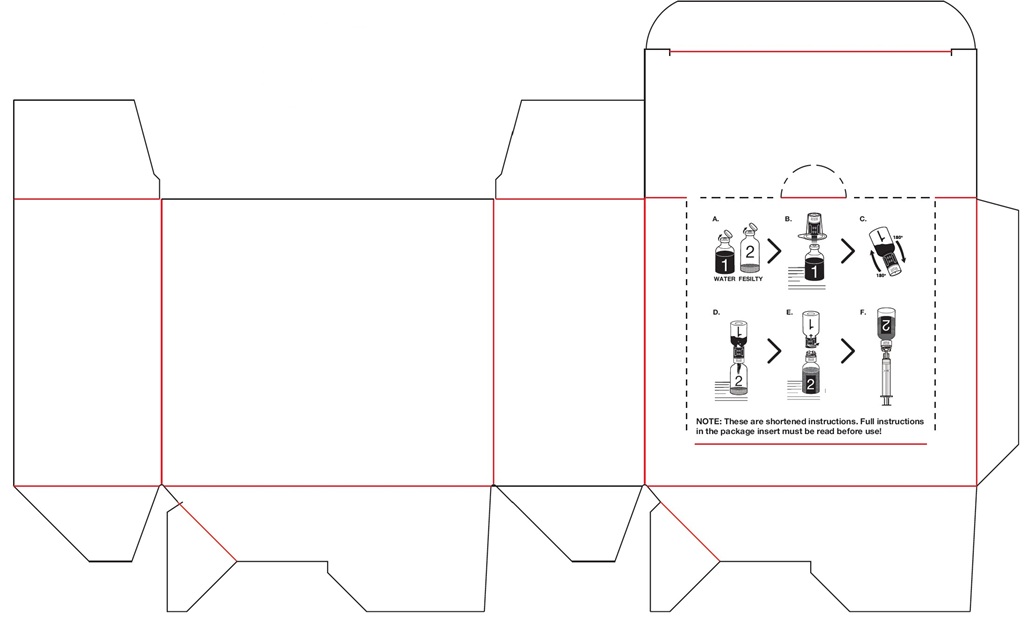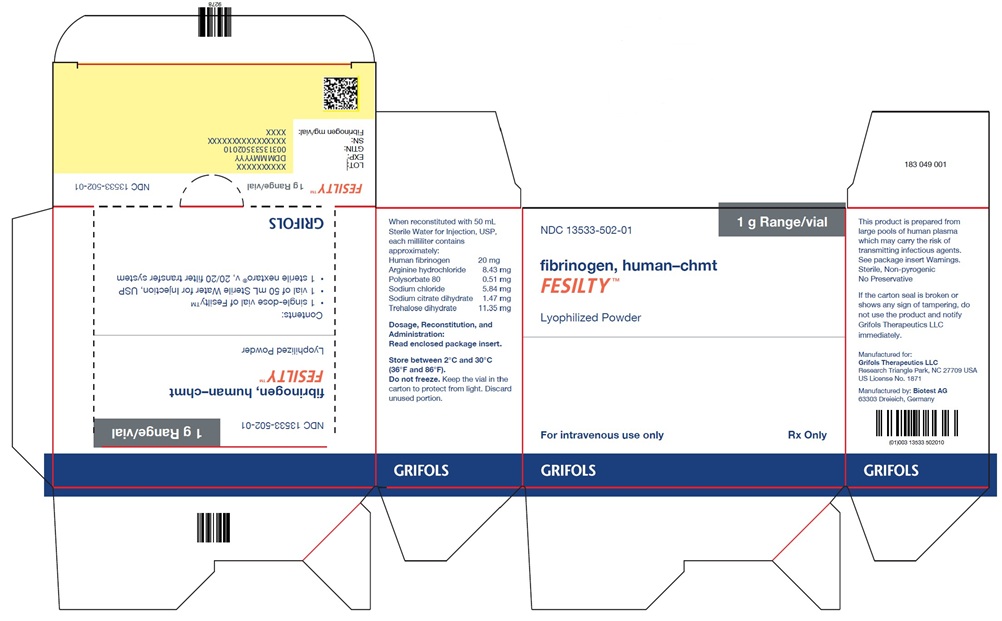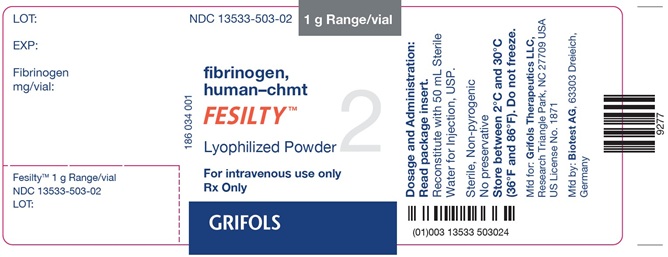 DRUG LABEL: FESILTY
NDC: 13533-502 | Form: KIT | Route: INTRAVENOUS
Manufacturer: Grifols USA LLC
Category: other | Type: PLASMA DERIVATIVE
Date: 20251230

ACTIVE INGREDIENTS: Fibrinogen Human 20 mg/1 mL
INACTIVE INGREDIENTS: Arginine Hydrochloride; Sodium Chloride; Trisodium Citrate Dihydrate; Polysorbate 80; Trehalose Dihydrate; Water

HIGHLIGHTS OF PRESCRIBING INFORMATION

These highlights do not include all the information needed to use FESILTY safely and effectively. See full prescribing information for FESILTY.
FESILTY (fibrinogen, human - chmt), lyophilized powder for reconstitution, for intravenous use
Initial U.S. Approval: 2025

1 INDICATIONS AND USAGE

FESILTY is a human blood coagulation factor indicated for the treatment of acute bleeding episodes in pediatric and adult patients with congenital fibrinogen deficiency, including hypo- or afibrinogenemia. (1)
Limitations of Use:
FESILTY is not indicated for dysfibrinogenemia. (1)

2 DOSAGE AND ADMINISTRATION

Intravenous use after reconstitution only.

- Calculate the dose in mg fibrinogen per kg of BW for each patient individually. The target plasma fibrinogen level is 100 mg/dL for minor bleeding and 150 mg/dL for major bleeding. (2.1)

When plasma fibrinogen level is known:

Patient Age | Calculation for Recommended Dose (mg/kg BW)
Adults and pediatric patients ≥ 6 years of age | [Target fibrinogen level (mg/dL) – Measured fibrinogen level (mg/dL)] /1.8 (mg/dL per mg/kg BW)
Pediatric patients < 6 years of age | [Target fibrinogen level (mg/dL) – Measured fibrinogen level (mg/dL)] /1.6 (mg/dL per mg/kg BW)

When plasma fibrinogen is not known:
Dose: 70 mg/kg BW for patients of all ages
Frequency and duration of dosing:

- Monitor fibrinogen levels. Individualize the frequency and duration of dosing based on the extent of bleeding, plasma fibrinogen level, and the clinical condition of the patient.
- Infuse FESILTY using an infusion pump at an infusion rate not to exceed 5 mL/min. Initial infusion rates are: (2.3)

Patient Age | Maximum Infusion Rate
Adults and pediatric patients ≥ 6 years of age | 5 mL/min
Pediatric patients 4 to < 6 years of age | 1.0 mL/min
Pediatric patients 2 to < 4 years of age | 0.75 mL/min
Pediatric patients 28 days to < 2 years of age | 0.30 mL/min
Newborns (0 to 27 days) | 0.10 mL/min

3 DOSAGE FORMS AND STRENGTHS

FESILTY is a sterile, lyophilized, white in color powder for solution for intravenous injection. FESILTY is provided as one single-dose glass vial containing nominally 1 gram of human fibrinogen and one 50 mL glass vial of Sterile Water for Injection, USP. The actual amount of fibrinogen in milligrams fibrinogen per vial is printed on the vial label and carton. (3)

4 CONTRAINDICATIONS

Severe hypersensitivity reactions, including anaphylaxis, to FESILTY or its components (arginine hydrochloride, polysorbate 80, sodium citrate dihydrate, trehalose dihydrate) (4)

5 WARNINGS AND PRECAUTIONS

- Hypersensitivity reactions have occurred in patients receiving FESILTY. Should symptoms occur, discontinue FESILTY and administer appropriate treatment. (5.1)
- Thrombotic events have been reported in patients receiving FESILTY. Weigh the benefits of administration versus the risks of thrombosis. (5.2)
- FESILTY is made from pooled human plasma and may carry the risk of transmitting infectious agents. All infections thought to be transmitted by FESILTY should be reported to Grifols at 1-800-520-2807, (5.3)

6 ADVERSE REACTIONS

The most common adverse reactions (incidence > 2%) were pain in extremity, back pain, hypersensitivity reactions, pyrexia, thrombosis, fibrin D dimer increased, headache, and vomiting. (6.1)
To report SUSPECTED ADVERSE REACTIONS, contact Grifols Therapeutics LLC at 1-800-520-2807 or FDA at 1-800-FDA-1088 or www.fda.gov/medwatch.

FULL PRESCRIBING INFORMATION

1 INDICATIONS AND USAGE

FESILTY is indicated for the treatment of acute bleeding episodes in pediatric and adult patients with congenital fibrinogen deficiency, including hypo- or afibrinogenemia.
Limitations of Use:
FESILTY is not indicated for dysfibrinogenemia.

2 DOSAGE AND ADMINISTRATION

2.1 Dose

For intravenous use after reconstitution only
The target plasma fibrinogen level is 100 mg/dL for minor bleeding and 150 mg/dL for major bleeding.
The actual amount of fibrinogen in milligrams per vial of FESILTY is printed on the vial label and carton.
FESILTY dose when baseline fibrinogen level is known
The dose for each patient must be individually calculated taking into consideration age, the location and extent of bleeding, the plasma level of fibrinogen (mg/dL), and the clinical condition of the patient.
Calculate the recommended dose in milligrams fibrinogen per kilogram BW according to the age of the patient:

- Adults and pediatric patients ≥ 6 years of age

Dose (mg/kg BW) = | Target fibrinogen level (mg/dL) – Measured fibrinogen level (mg/dL)
Dose (mg/kg BW) = | 1.8 (mg/dL per mg/kg BW)

- Pediatric patients < 6 years of age

Dose (mg/kg BW) = | Target fibrinogen level (mg/dL) – Measured fibrinogen level (mg/dL)
Dose (mg/kg BW) = | 1.6 (mg/dL per mg/kg BW)

Monitor plasma fibrinogen level and repeat the dose if the plasma fibrinogen level drops below the target level until hemostasis is achieved.
Individualize the frequency and duration of dosing based on the extent of bleeding, plasma fibrinogen level, and the clinical condition of the patient.
FESILTY dose when baseline fibrinogen level is not known
The recommended dose when the baseline fibrinogen is not known is 70 mg/kg BW for patients of all ages.
Monitor plasma fibrinogen level and repeat the dose as needed to maintain the target fibrinogen level.
Individualize the frequency and duration of dosing based on the extent of bleeding, plasma fibrinogen level, and the clinical condition of the patient.

2.2 Preparation and Reconstitution

FESILTY is a white powder. Upon reconstitution with sterile water, the solution is almost colorless and clear to slightly opalescent.
The following procedures are provided as a guide for the preparation and reconstitution of FESILTY.
Preparation
Inspect the carton kit before opening. Discard the kit if the package is damaged or if the seal on the carton shows signs of tampering.
Do not use FESILTY after the expiration date printed on the vial label and carton.
If stored refrigerated, allow the unopened vials of Sterile Water for Injection, USP (vial number 1) and product (FESILTY, vial number 2) to come to room temperature.
Use aseptic technique (clean and sanitized) and a flat surface during reconstitution of FESILTY.
Reconstitution with nextaro® v, 20/20 5 µm transfer system

1. Remove the caps from the water vial and the product vial in order to expose the central portions of the stoppers (Fig. 1). Cleanse each vial stopper with an alcohol swab and allow surface to dry.
2. Completely remove the paper seal of the transfer system blister package (Fig. 2). To maintain sterility, keep the transfer device in the clear blister package. Do not touch the spike.
3. Place the water vial on an even surface. Place the blue part of the transfer system within the blister straight onto the upright water vial (Fig. 3) until it snaps into place. Do not twist the transfer system.
4. Remove the clear part of the blister package from the transfer system. Now the white part of the transfer system is visible (Fig. 4).
5. Place the product vial on an even surface.
6. Turn the combination of transfer system and water vial upside down (Fig. 5). Push the spike of the white end of the transfer system straight down through the product vial stopper (Fig. 6) until it snaps into place. The vacuum present in the product vial causes the water to flow into the product vial (Fig. 7). Wait until water transfer is complete.
7. Gently sway the unit consisting of the transfer system, product and water vial, to dissolve the powder. Do not shake the unit, to avoid foaming. The powder should be dissolved completely within approximately 3 minutes. Discard the product if the powder is not fully dissolved within 30 minutes. After reconstitution the solution should be clear or slightly opalescent.
8. Afterwards unscrew the blue part of the transfer system together with the empty water vial counterclockwise (Fig. 8). Discard the water vial with the blue part of the transfer system attached. The luer-lock connector is now visible. To maintain sterility do not touch the luer-lock connector.
9. The solution is ready for use. Keep the solution at room temperature and use within 4 hours after dissolving. Do not use solutions that are cloudy or contain visible particles.
10. Screw a sterile syringe (not supplied) onto the luer-lock connector of the product vial with the white part of the transfer system and invert (Fig. 9) to allow you to easily draw the dissolved drug into the syringe. Use constant force during drawing to avoid foaming. A separate filter is not necessary because the transfer system has its own integrated filter.
11. Carefully disconnect the vial with the white part of the transfer system from the syringe. A standard infusion set is recommended for intravenous injection of the solution.
12. If the dose requires more than one vial of FESILTY, reconstitute each vial using a new nextaro® v, 20/20 transfer system provided in the carton. The nextaro® v, 20/20 transfer system is for single use only.

Do not shake.
Do not mix FESILTY with other intravenous medications. Administer by a separate injection/infusion line.
FESILTY is for single use only. It contains no preservatives.
Discard unused portion.

2.3 Administration

Inspect visually for particulate matter and discoloration prior to administration. Do not use if the liquid is cloudy or turbid, discolored, or if it contains visible particulate matter.
Infusion Rates
Infuse FESILTY intravenously using an infusion pump at an infusion rate not to exceed 5 mL/min. The initial infusion rates are provided in Table 1. Selection of the infusion rate remains principally at the discretion of the treating physician considering the exact clinical situation of the patient.

Table 1: Infusion Rates for FESILTY
Patient Age | Initial Infusion Rate [Infusion rate not to exceed 5 mL/min]
Adults and pediatric patients ≥ 6 years of age | 5 mL/min
Pediatric patients 4 to < 6 years of age | 1.0 mL/min
Pediatric patients 2 to < 4 years of age | 0.75 mL/min
Pediatric patients 28 days to < 2 years of age | 0.30 mL/min
Newborns (0 to 27 days) | 0.10 mL/min

3 DOSAGE FORMS AND STRENGTHS

FESILTY is a sterile, lyophilized, white in color powder for solution for intravenous injection. FESILTY is provided as one single-dose glass vial containing nominally 1 gram of human fibrinogen and one 50 mL glass vial of Sterile Water for Injection, USP. The actual amount of fibrinogen in milligrams of fibrinogen per vial is printed on the vial label and carton.

4 CONTRAINDICATIONS

FESILTY is contraindicated in patients who have severe hypersensitivity reactions, including anaphylaxis, to FESILTY or its components (arginine hydrochloride, polysorbate 80, sodium citrate dihydrate, trehalose dihydrate). [see Warnings and Precautions (5.1)]

5 WARNINGS AND PRECAUTIONS

5.1 Hypersensitivity

Hypersensitivity reactions have occurred to FESILTY or its components (arginine hydrochloride, polysorbate 80, sodium citrate dihydrate, trehalose dihydrate). Monitor patients for signs and symptoms of hypersensitivity reactions including hives, generalized urticaria, tightness of the chest, wheezing, hypotension, and anaphylaxis. If symptoms occur, discontinue FESILTY infusion immediately. Manage patients based on clinical practice accordingly.

5.2 Thrombosis

Thrombotic events have occurred in patients receiving FESILTY [see Adverse Reactions (6)]. Thrombosis may occur spontaneously in patients with congenital fibrinogen deficiency with or without the use of fibrinogen replacement therapy. Weigh the benefits of FESILTY administration versus the risks of thrombosis. Monitor patients receiving FESILTY for signs and symptoms of thrombosis.

5.3 Transmissible Infectious Agents

Because FESILTY is made from pooled human plasma, it may carry a risk of transmitting infectious agents, e.g., viruses, the variant Creutzfeldt-Jakob disease (vCJD) agent and, theoretically, the Creutzfeldt-Jakob disease (CJD) agent. This also applies to unknown or emerging viruses and other pathogens. The risk of infectious agent transmission has been reduced by screening plasma donors and by including virus inactivation as well as virus and prion removal steps in the manufacturing process of FESILTY[see Description (11)].
All infections suspected to have been transmitted by FESILTY should be reported by the physician or other healthcare provider to Grifols at 1-800-520-2807.

6 ADVERSE REACTIONS

6.1 Clinical Trials Experience

Because clinical trials are conducted under widely varying conditions, adverse reaction rates observed in the clinical trials of one drug cannot be directly compared to rates in the clinical trials of another drug and may not reflect the rates observed in clinical practice.
The safety data described in this section reflects exposure to FESILTY in one clinical study (Study 984). A total of 45 patients with congenital fibrinogen deficiency received at least one dose of FESILTY. A total of 175 bleeding episodes were treated with a mean dose of 3.9 g [see Clinical Studies (14)].
Serious adverse reactions occurred in 4 patients (9%) including portal vein thrombosis (n=1), deep vein thrombosis (n=1), and pain in extremity with clinically suspected thrombosis (n=1). One patient had episode of epilepsy and died due to extradural hematoma four weeks after FESILTY administration.
Table 2 lists the most common adverse reactions that occurred in > 2% patients in Study 984.

Table 2: Adverse Reactions Occurring in > 2% Patients in Study 984
Adverse Reaction | N=45 n (%)
Pain in extremity | 3 (7)
Back pain | 3 (7)
Hypersensitivity reactions [Hypersensitivity reactions = all patients had adverse reactions of facial swelling.] | 3 (7)
Pyrexia | 2 (4)
Thrombosis [Thrombosis includes portal vein thrombosis and deep vein thrombosis.] | 2 (4)
Fibrin D dimer increased | 2 (4)
Headache | 2 (4)
Vomiting | 2 (4)

8 USE IN SPECIFIC POPULATIONS

8.1 Pregnancy

Risk Summary
No human data are available to indicate the presence or absence of a drug-associated risk. Animal reproduction studies have not been conducted with FESILTY. One patient in clinical trial 984 reported pregnancy 11 months after receiving FESILTY. The patient withdrew from the study and there were no reports of complications during the pregnancy. It is not known whether FESILTY can cause fetal harm when administered to a pregnant woman or can affect fertility.
In the U.S. general population, the estimated background risk of major birth defects and miscarriage in clinically recognized pregnancies is 2-4% and 15-20% respectively.

8.2 Lactation

Risk Summary
There is no information regarding the presence of FESILTY in breast milk, the effect on the breast-fed infant, or the effects on milk production. The developmental and health benefits of breast feeding should be considered along with the mother’s clinical need for FESILTY and any potential adverse effects on the breast-fed infant from FESILTY or from the underlying maternal condition.

8.4 Pediatric Use

The safety and effectiveness of FESILTY have been established in pediatric patients with congenital fibrinogen deficiency. Use of FESILTY in pediatric patients was supported by evidence from one clinical study (Study 984) that enrolled 24 pediatric patients 0 to 16 years of age (6 patients aged 0 to < 6 years, 18 patients aged ≥6 years) with congenital fibrinogen deficiency [see Adverse Reactions (6) and Clinical Studies (14)].

8.5 Geriatric Use

Clinical study of FESILTY in patients with congenital fibrinogen deficiency did not include patients aged 65 years and over to provide evidence as to whether or not they respond differently than younger patients.

11 DESCRIPTION

FESILTY (fibrinogen, human – chmt), is a purified, sterile, non-pyrogenic, lyophilized powder of human fibrinogen for reconstitution for intravenous administration. Human fibrinogen is purified from Source Plasma from the cryoprecipitate fraction and processed using a combination of aluminum hydroxide purification, solvent/detergent (S/D) treatment, anion and cation exchange chromatography, glycine precipitation, and Ultraviolet (UV)-C irradiation. FESILTY is supplied in a single-dose vial containing nominally 1 gram of fibrinogen. The actual amount of fibrinogen is printed on the vial label and carton in milligrams fibrinogen per vial. When reconstituted with 50 mL sterile water for injection, FESILTY contains approximately 20 mg/mL protein, of which not less than 80% is fibrinogen monomer. Each vial of FESILTY also contains 421.3 mg arginine hydrochloride, 292.2 mg sodium chloride, 73.5 mg sodium citrate dihydrate, 25.5 mg polysorbate 80, and 567.5 mg trehalose dihydrate. FESILTY has a pH of 6.5 to 7.5 and an osmolality of ≥ 240 mOsmol/kg. FESILTY does not contain preservatives and is not made with natural rubber latex.
FESILTY is prepared from pooled Source Plasma obtained from healthy volunteer donors. Each plasma donation used for the manufacture of FESILTY is collected from FDA-licensed facilities. Plasma donations must test negative for hepatitis B virus (HBV) surface antigen (HBsAg), antibodies to human immunodeficiency virus (HIV) strains 1 and 2 (anti-HIV-1/2), and antibodies to the hepatitis C virus (anti-HCV) as determined by enzyme immunoassay (EIA). In addition, samples from manufacturing pools must test non-reactive for HIV RNA, HCV RNA, HBV DNA, and Hepatitis A Virus (HAV) RNA, by Nucleic Acid Amplification Testing (NAT). Parvovirus B19 (B19V) DNA is also tested by NAT and must not exceed 10^4 IU/mL in the manufacturing pool.
The manufacturing process for FESILTY employs several steps to remove/inactivate adventitious viruses to further increase the margins of safety. These steps include S/D treatment, UV-C irradiation, and heat treatment of lyophilized fibrinogen. Virus clearance studies with a scaled-down process have been performed for these steps to determine their capacity to inactivate or remove both enveloped and non-enveloped viruses. The results are shown in Table 3.

Table 3: Virus Reduction Factors (log10) during FESILTY Manufacturing Process for Enveloped (E) and Non-enveloped (NE) Viruses
Step | HIV [HIV: Human immunodeficiency virus] (E) | PRV [PRV: Porcine pseudorabies virus (varicellovirus suidalpha 1), a generic model for hepatitis B virus] (E) | BVDV [BVDV: Bovine viral diarrhea virus 1 (pestivirus bovis), a model for hepatitis C virus (hepacivirus hominis)] (E) | HAV [HAV: Hepatitis A virus (hepatovirus A)] (NE) | PPV [PPV: Porcine parvovirus (protoparvovirus ungulate 1), a model for human parvovirus B19 (erythroparvovirus primate1)] (NE)
S/D [S/D: Solvent/detergent] Treatment | ≥ 4.51 | ≥ 5.39 | ≥ 5.21 | n.d. [n.d.: Not determined] | n.d.
UV-C [UVC: Ultraviolet-C] Irradiation | n.d. | 1.63 | 1.87 | 2.47 | 4.19
Lyophilization & Dry Heat Treatment | ≥ 4.86 | ≥ 5.36 | ≥ 4.29 | ≥ 4.34 | 1.09
Total Clearance | ≥ 9.37 | ≥ 12.38 | ≥ 11.37 | ≥ 6.81 | 5.28

The manufacturing process was also investigated for its capacity to reduce the infectivity of an experimental agent of transmissible spongiform encephalopathy (TSE), considered a model for CJD and its variant, vCJD. One chromatographic purification step has been shown to reduce TSE infectivity of an experimental model agent. These studies provide reasonable assurance that low levels (at least 3.27 log10) of vCJD/CJD agent infectivity, if present in the starting material, would be removed.

12 CLINICAL PHARMACOLOGY

12.1 Mechanism of Action

Fibrinogen (Factor I) is a soluble plasma protein that, during the coagulation process, is converted to fibrin, one of the key components of the blood clot. Fibrinogen is a heterohexamer with a molecular weight of 340 kDa and composed of two sets of alpha, beta, and gamma polypeptide chains.
Fibrinogen plays a fundamental role in achieving and maintaining overall hemostasis. Following coagulation activation and thrombin generation, fibrinogen is cleaved by thrombin at specific sites on the alpha and beta chains to remove fibrinopeptide A (FPA) and fibrinopeptide B (FPB). The removal of FPA and FPB exposes binding sites on the fibrinogen molecule and leads to the formation of fibrin monomers that subsequently undergo polymerization. The resulting fibrin is stabilized by activated factor XIII which forms cross links between fibrin polymers and renders the fibrin clot more resistant to fibrinolysis. Additionally, soluble fibrinogen mediates platelet aggregation by binding to the glycoprotein IIb/IIIa (GPIIb/IIIa) receptor on the platelet surface activated following blood vessel injury. This interaction acts as a bridge between platelets, facilitating their aggregation, i.e., formation of primary platelet plug. The end product of the coagulation cascade, cross-linked fibrin, stabilizes and reinforces the primary platelet plug to achieve secondary hemostasis and stop bleeding.

12.2 Pharmacodynamics

In a prospective, open-label, multicenter phase I clinical trial the pharmacodynamic properties for FESILTY were evaluated in 27 patients of all age groups with congenital afibrinogenemia or severe hypofibrinogenemia. The assessment was based on fibrinogen activity (FiAc) levels in plasma after a single intravenous administration of 70 mg/kg BW. Maximum clot firmness (MCF) was measured by thromboelastometry and showed a positive correlation with FiAc levels of FESILTY in patients across the age groups.

12.3 Pharmacokinetics

PK properties of FESILTY were investigated based on FiAc levels in plasma after a single intravenous administration of 70 mg/kg BW in patients with congenital afibrinogenemia or severe hypofibrinogenemia of all age groups.

Table 4: Summary of Pharmacokinetic Parameters for FESILTY Fibrinogen Activity (FiAc) by Age Groups
Parameters [Pharmacokinetic parameters are summarized as Mean (Standard Deviation).] | Overall N=17 | 6 to < 12 years N = 1 | 12 to < 18 years N = 2 | 18 to 75 years N = 14
t1/2 [h] | 54.8 (13.4) | 63.1 | 57.4 (25.7) | 53.8 (12.7)
Cmax [g/L] | 1.47 (0.4) | 1.74 | 1.16 (0.5) | 1.49 (0.4)
AUC0-∞ [g*h/L)] | 97.8 (39.1) | 92.8 | 79.4 (52.1) | 101 (40.1)
MRT0-∞ [h] | 80.3 (19.3) | 88.6 | 84.8 (39.3) | 79.1 (18.1)
Vdss per kg [mL/kg] | 62.2 (16.3) | 66.8 | 80.8 (18.5) | 59.2 (15.4)
CL per kg (mL/[h*kg]) | 0.836 (0.4) | 0.754 | 1.13 (0.7) | 0.801 (0.3)
IR (mg/dL per mg/kg dose) | 2.10 (0.6) | 2.49 | 1.66 (0.7) | 2.13 (0.6)
Abbreviations: AUC0-∞ = area under the curve (AUC) from time 0 to infinity; Cmax = maximum concentration; CL = clearance; IR = incremental recovery based on observations; MRT0-∞ = mean residence time extrapolated toinfinity; N = number of patients; t1/2 = half-life; Vdss = volume of distribution at steady state.
Data reflects subjects in Study 984 with a minimum of five observations.

A population pharmacokinetic model was developed that pooled the data collected in 27 patients aged 1 to 40 years who received 70 mg/kg of FESILTY. A two-compartment model was used for integrated assessments of FiAg and FiAc levels, with body weight included as a covariate to describe the pharmacokinetic data. The analysis demonstrated that the median AUC0-239h of FiAc was lower by 27.6% in patients aged < 6 years, by 13.6% in patients aged 6 to < 12 years, and by 3.4% in patients aged 12 to < 18 years compared to adult patients. The median Cmax was comparable between pediatric and adult patients.

14 CLINICAL STUDIES

The efficacy of FESILTY was evaluated in an open-label, single arm, multicenter, study (Study 984; NCT 02065882) in patients with congenital hypo- or afibrinogenemia. Patients with dysfibrogenemia were excluded. The study assessed FESILTY for on-demand treatment (ODT) and for on-demand prophylaxis (ODP) of bleeding events.
A total of 36 patients received FESILTY for 175 bleeding events. The median number of FESILTY infusions per bleeding event was 1 (range: 1 to 6). The mean total perioperative dose of FESILTY for 54 surgical bleeding events was 70.3 mg/kg BW for adults and 125.9 mg/kg BW for pediatric patients. The mean dose for 175 bleeding events was 70.1 mg/kg for adults and 75.8 mg/kg for pediatric patients.
The demographic characteristics of the study population were as follows: The median age was 18 years (range: 1 to 46 years) including 3 patients aged 0 to < 6 years, 9 patients aged 6 to < 12 years, and 4 patients aged 12 to < 18 years. Twenty-two patients (61%) were male and 36 patients (100%) were White. Thirty-four patients (94%) had congenital afibrinogenemia and two patients (6%) had severe hypofibrinogenemia. Out of 175 bleeding events, 45 were traumatic, 65 were spontaneous, 54 were surgical and 11 bleeds were classified as “other”. There were 60 bleeds treated with ODP and 115 bleeds with ODT.
The main efficacy endpoint was the overall hemostatic response (OHR) based on a 4-point scale assessed by the investigator as excellent, good, moderate or none. The other efficacy endpoint was the mean change in maximum clot formation (MCF) at 1 hour after infusion.
The OHR for 175 bleeding events in 36 patients was reported as excellent in 150 bleeding events (86%), good in 23 bleeding events (13%), and moderate in 2 bleeding events (1%). The mean change in MCF was 10.76 mm at 1 hour after FESILTY infusion.

16 HOW SUPPLIED/STORAGE AND HANDLING

FESILTY is supplied in a kit containing one single-dose glass vial of human fibrinogen, one glass vial of 50 mL Sterile Water for Injection, USP, and one nextaro® v, 20/20 sterile transfer system.

Carton NDC | Container NDC | Fibrinogen Content
13533-502-01 | 13533-503-02 | approximately 1 gram

The actual amount of human fibrinogen in milligrams per vial is printed on the vial label and carton.

- FESILTY is not made with natural rubber latex.
- Keep FESILTY in its original carton to protect it from light.
- Store between 2oC and 30oC (36oF and 86oF). Do not freeze.
- Do not use after expiration date printed on the vial label and carton.
- Use within 4 hours after reconstitution.
- Discard unused portion.

17 PATIENT COUNSELING INFORMATION

Discuss following with the patient and/or caregiver:

- Hypersensitivity reactions: Inform patients and/or caregiver of the early signs of hypersensitivity reactions to FESILTY (including hives, generalized urticaria, tightness of the chest, wheezing, hypotension, and anaphylaxis), and advise them to notify their physician immediately if they experience any of these symptoms [see Warnings and Precautions (5.1)].
- Thrombosis: Inform patients and/or caregiver that blood clots with or without consequent obstruction of blood flow may occur with FESILTY. Any symptoms of blood clots such as unexplained chest and/or leg pain or swelling of the legs or arms, coughing up blood, shortness of breath, increased rate of breathing or unexplained symptoms related to the nervous system such as stroke or weakness following administration of FESILTY should be reported to their physician immediately [see Warnings and Precautions (5.2)].
- Transmission of infectious agents: Inform patients and/or caregiver that because FESILTY is made from pooled human plasma, it may carry a risk of transmitting infectious agents that can cause disease (e.g., viruses, vCJD agent, and theoretically, the CJD agent). Explain that the risk that FESILTY may transmit an infection has been reduced by screening plasma donors for prior exposure, testing donated plasma, and inactivating or removing certain viruses during manufacturing, patients should report any symptoms that concern them [see Description (11), Warnings and Precautions (5.3)].

Manufactured by:
Biotest AG
63303 Dreieich, Germany
Manufactured for:
Grifols Therapeutics LLC
Research Triangle Park, NC 27709 USA
US License No. 1871

PACKAGE LABEL.PRINCIPAL DISPLAY PANEL

NDC 13533-503-02 1 g Range/vial
fibrinogen,
human-chmt
FESILTY™
Lyophilized Powder 2
For intravenous use only
Rx Only
GRIFOLS
Dosage and Administration:
Read package insert.
Reconstitute with 50 mL Sterile
Water for Injection, USP.
Sterile, Non-pyrogenic
No preservative
Store between 2°C and 30°C
(36°F and 86°F). Do not freeze.
Mfd for: Grifols Therapeutics LLC,
Research Triangle Park, NC 27709 USA
US License No. 1871
Mfd by: Biotest AG, 63303 Dreieich,
Germany
(01)003 13533 503024
LOT:
EXP:
Fibrinogen
mg/vial:
Fesilty™ 1 g Range/vial
NDC 13533-503-02
LOT:
186 034 001

NDC 13533-200-50 Rx Only
Sterile Water for
Injection, USP
For reconstitution of
accompanying product
Single-Dose Container. 1
GRIFOLS 50 mL
Nonpyrogenic. Do not use unless
clear. No antimicrobial agent or
other substance has been added.
Do not use for intravascular injection
without making approximately
isotonic by addition of suitable
solute. Discard unused portion.
Mfd by: Laboratorios Grifols S. A., Parets del Vallès,
Barcelona, 08150 Spain
LOT:
EXP:
186 036 001
(01)003 13533 200503

NOTE: These are shortened instructions. Full instructions
in the package insert must be read before use!

NDC 13533-502-01 1 g Range/vial
fibrinogen human-chmt
FESILTY™
Lyophilized Powder
For intravenous use only Rx Only
GRIFOLS
This product is prepared from
large pools of human plasma
which may carry the risk of
transmitting infectious agents.
See package insert Warnings.
Sterile, Non-pyrogenic
No Preservative
If the carton seal is broken or
shows any sign of tampering, do
not use the product and notify
Grifols Therapeutics LLC
immediately.
Manufactured for:
Grifols Therapeutics LLC
Research Triangle Park, NC 27709 USA
US License No. 1871
Manufactured by: Biotest AG
63303 Dreieich, Germany
(01)003 13533 502010
GRIFOLS
183 049 001
When reconstituted with 50 mL
Sterile Water for Injection, USP,
each vial contains
approximately:
Human fibrinogen 20 mg
Arginine hydrochloride 8.43 mg
Polysorbate 80 0.51 mg
Sodium chloride 5.84 mg
Sodium citrate dihydrate 1.47 mg
Trehalose dihydrate 11.35 mg
Dosage, Reconstitution, and
Administration:
Read enclosed package insert.
Store between 2°C and 30°C
(36°F and 86°F).
Do not freeze. Keep the vial in the
carton to protect from light. Discard
unused portion.
GRIFOLS
NDC 13533-502-01
1 g Range/vial
fibrinogen, human-chmt
FESILTY™
Lyophilized Powder
Contents:

- 1 single-dose vial of Fesilty™
- 1 vial of 50 mL Sterile Water for Injection, USP
- 1 sterile nextaro® v, 20/20 filter transfer system

GRIFOLS
FESILTY™ 1 g Range/vial NDC 13553-502-01

LOT: XXXXXXXXXX
EXP: DDMMMYYYY
GTIN: 00313533502010
SN: XXXXXXXXXXXXXXXX
Fibrinogen mg/vial: XXXX